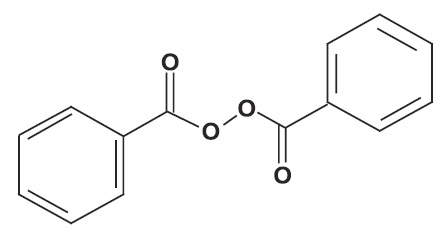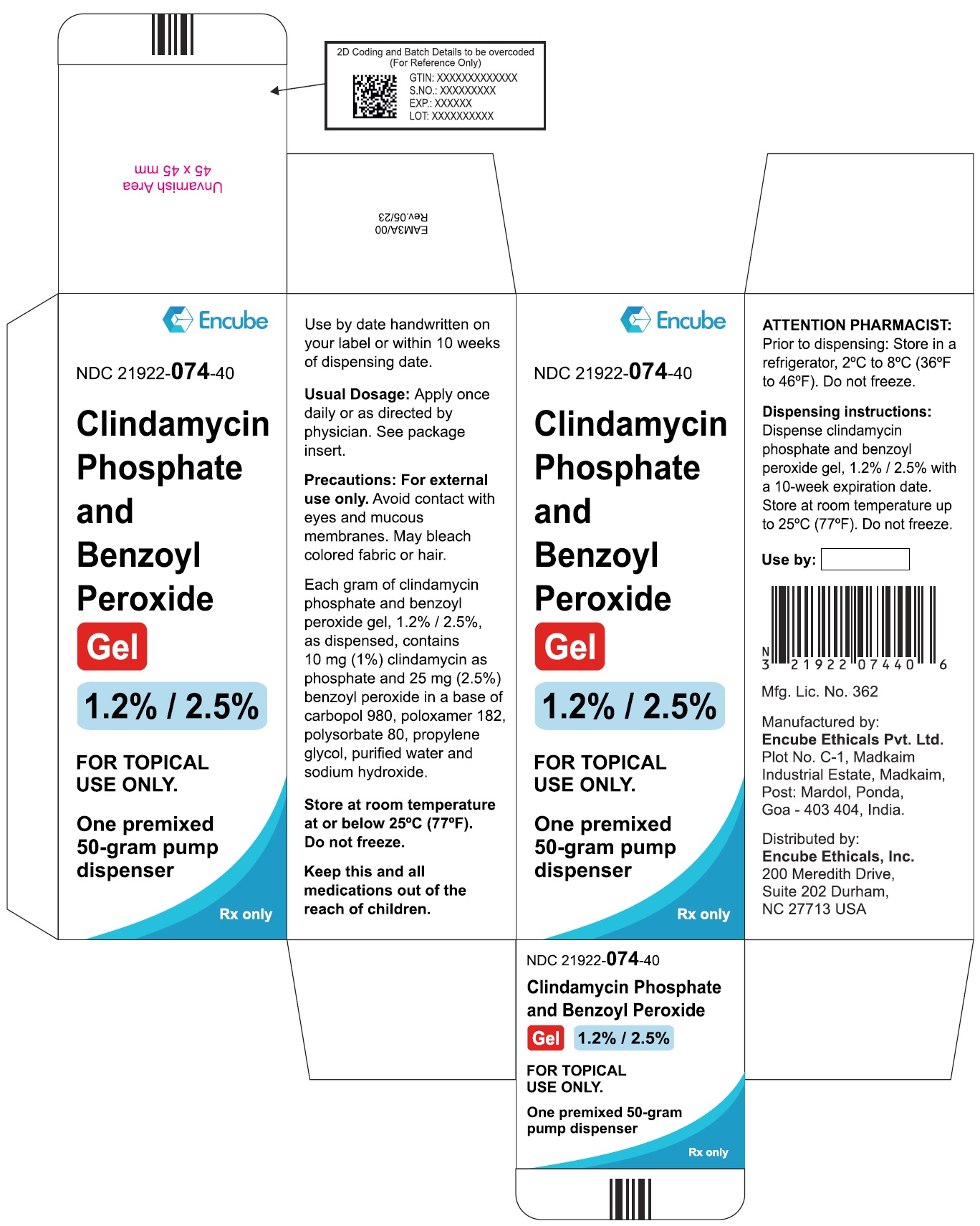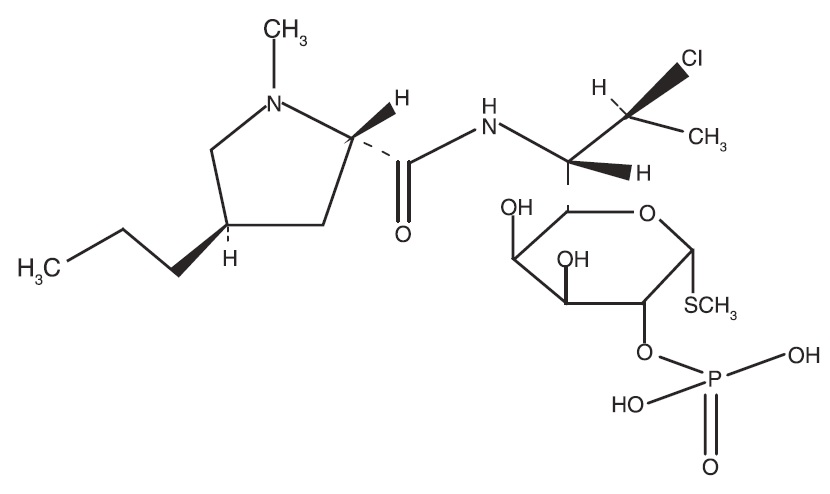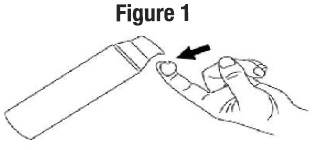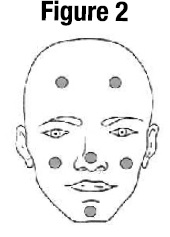 DRUG LABEL: CLINDAMYCIN PHOSPHATE AND BENZOYL PEROXIDE
NDC: 21922-074 | Form: GEL
Manufacturer: Encube Ethicals, Inc.
Category: prescription | Type: Human Prescription Drug Label
Date: 20250930

ACTIVE INGREDIENTS: CLINDAMYCIN PHOSPHATE 10 mg/1 g; BENZOYL PEROXIDE 25 mg/1 g
INACTIVE INGREDIENTS: POLOXAMER 182; PROPYLENE GLYCOL; POLYSORBATE 80; CARBOMER HOMOPOLYMER TYPE C (ALLYL PENTAERYTHRITOL CROSSLINKED); SODIUM HYDROXIDE; WATER

HIGHLIGHTS OF PRESCRIBING INFORMATION

These highlights do not include all the information needed to use CLINDAMYCIN PHOSPHATE AND BENZOYL PEROXIDE GEL, 1.2%/ 2.5% safely and effectively. See full prescribing information for CLINDAMYCINPHOSPHATE AND BENZOYL PEROXIDE GEL, 1.2% / 2.5%.
CLINDAMYCIN PHOSPHATE AND BENZOYL PEROXIDE Gel,1.2% / 2.5%
For topical use
Initial U.S. Approval: 2000

1 INDICATIONS AND USAGE

Clindamycin Phosphate and Benzoyl Peroxide Gel, 1.2% / 2.5% is a lincosamide antibiotic and benzoyl peroxide indicated for the topical treatment of acne vulgaris. (1)

2 DOSAGE AND ADMINISTRATION

• Apply a pea-sized amount of Clindamycin Phosphate and Benzoyl Peroxide Gel, 1.2% / 2.5% to the face once daily. (2)
• Not for oral, ophthalmic, or intravaginal use. (2)

3 DOSAGE FORMS AND STRENGTHS

• Clindamycin Phosphate and Benzoyl Peroxide Gel, 1.2% / 2.5% contains clindamycin phosphate 1.2% and benzoyl peroxide 2.5% in a topical gel in 50 gram pumps. (3)

4 CONTRAINDICATIONS

Clindamycin Phosphate and Benzoyl Peroxide Gel,1.2% / 2.5% is contraindicated in:
• Patients who have demonstrated hypersensitivity (e.g., anaphylaxis) to clindamycin, benzoyl peroxide, any components of the formulation, or lincomycin. (4)
• Patients with a history of regional enteritis, ulcerative colitis, or antibiotic–associated colitis. (4)

5 WARNINGS AND PRECAUTIONS

• Colitis: Orally and parenterally administered clindamycin has been associated with severe colitis, which may result in death. Diarrhea, bloody diarrhea, and colitis (including pseudomembranous colitis) have been reported with the use of topical and systemic clindamycin. Clindamycin Phosphate and Benzoyl Peroxide Gel, 1.2% / 2.5% should be discontinued if significant diarrhea occurs. (5.1)
• Ultraviolet Light and Environmental Exposure: Minimize sun exposure following drug application. (5.2)

6 ADVERSE REACTIONS

The following selected adverse reactions occurred in less than 0.2% of patients: application site pain (0.1%); application site exfoliation (0.1%); and application site irritation (0.1%). (6.1)
To report SUSPECTED ADVERSE REACTIONS, contact Encube Ethicals Private Limited at 1-833-285-4151 or FDA at 1-800-FDA-1088 or www.fda.gov/medwatch

7 DRUG INTERACTIONS

• Clindamycin Phosphate and Benzoyl Peroxide Gel, 1.2% / 2.5% should not be used in combination with erythromycin containing products because of its clindamycin component. (7.1)

FULL PRESCRIBING INFORMATION

1 INDICATIONS AND USAGE

Clindamycin Phosphate and Benzoyl Peroxide Gel, 1.2% / 2.5% is indicated for the topical treatment of acne vulgaris in patients 12 years or older.

2 DOSAGE AND ADMINISTRATION

Apply a pea-sized amount of Clindamycin Phosphate and Benzoyl Peroxide Gel, 1.2% / 2.5% to the face once daily.
Use of Clindamycin Phosphate and Benzoyl Peroxide Gel, 1.2% / 2.5% beyond 12 weeks has not been evaluated.

Concomitant topical acne therapy should be used with caution because a possible cumulative irritancy effect may occur, especially with the use of peeling, desquamating, or abrasive agents.
Clindamycin Phosphate and Benzoyl Peroxide Gel, 1.2% / 2.5% is not for oral, ophthalmic, or intravaginal use.

3 DOSAGE FORMS AND STRENGTHS

Gel, 1.2% / 2.5%
Each gram of Clindamycin Phosphate and Benzoyl Peroxide Gel, 1.2% / 2.5% contains 10 mg (1%) clindamycin as phosphate, and 25 mg (2.5%) benzoyl peroxide in a white to off-white, opaque, smooth gel.

4 CONTRAINDICATIONS

4.1 Hypersensitivity

Clindamycin Phosphate and Benzoyl Peroxide Gel, 1.2% / 2.5% is contraindicated in those individuals who have shown hypersensitivity to clindamycin, benzoyl peroxide, any components of the formulation, or lincomycin. Anaphylaxis, as well as allergic reactions leading to hospitalization, has been reported in postmarketing use with Clindamycin Phosphate and Benzoyl Peroxide Gel, 1.2% / 2.5%. [See Postmarketing Experience (6.2).]

4.2 Colitis/Enteritis

Clindamycin Phosphate and Benzoyl Peroxide Gel, 1.2% / 2.5% is contraindicated in patients with a history of regional enteritis, ulcerative colitis, or antibiotic-associated colitis. [see Warnings and Precautions(5.1)].

5 WARNINGS AND PRECAUTIONS

5.1 Colitis

Systemic absorption of clindamycin has been demonstrated following topical use of clindamycin. Diarrhea, bloody diarrhea, and colitis (including pseudomembranous colitis) have been reported with the use of topical and systemic clindamycin. When significant diarrhea occurs, Clindamycin Phosphate and Benzoyl Peroxide Gel, 1.2% / 2.5% should be discontinued.

Severe colitis has occurred following oral and parenteral administration of clindamycin with an onset of up to several weeks following cessation of therapy. Antiperistaltic agents such as opiates and diphenoxylate with atropine may prolong and/or worsen severe colitis. Severe colitis may result in death.

Studies indicate toxin(s) produced by Clostridia is one primary cause of antibiotic-associated colitis. The colitis is usually characterized by severe persistent diarrhea and severe abdominal cramps and may be associated with the passage of blood and mucus. Stool cultures for Clostridium difficile and stool assay for C. difficile toxin may be helpful diagnostically.

5.2 Ultraviolet Light and Environmental Exposure

Minimize sun exposure including use of tanning beds or sun lamps following drug application [See Nonclinical Toxicology (13.1)].

6 ADVERSE REACTIONS

6.1 Clinical Trials Experience

Because clinical trials are conducted under prescribed conditions, adverse reaction rates observed in the clinical trial may not reflect the rates observed in practice. Because clinical trials are also conducted under widely varying conditions, adverse reactions observed in the clinical trials of a drug cannot always be directly compared to rates in the clinical trials of another drug and may not reflect the rates observed in practice.

The following selected adverse reactions occurred in less than 0.2% of patients treated with Clindamycin Phosphate and Benzoyl Peroxide Gel, 1.2% / 2.5%: application site pain (0.1%); application site exfoliation (0.1%); and application site irritation (0.1%).

During clinical trials, subjects were assessed for local cutaneous signs and symptoms of erythema, scaling, itching, burning and stinging. Most local skin reactions increased and peaked around week 4 and continually decreased over time reaching near baseline levels by week 12. The percentage of subjects that had symptoms present before treatment, the maximum value recorded during treatment, and the percent with symptoms present at week 12 are shown in Table 1.

Table 1: Local Skin Reactions - Percent of Subjects with Symptoms
Present. Combined Results from the Two Phase 3 Trials (N = 773)

 | Before Treatment (Baseline) |  |  | Maximum During Treatment |  |  | End of Treatment (Week 12)
 | Mild Mod.* Severe |  |  | Mild Mod.* Severe |  |  | Mild Mod.* Severe
Erythema | 22 | 4 | 0 | 25 | 5 | <1 | 15 | 2 | 0
Scaling | 8 | <1 | 0 | 18 | 3 | 0 | 8 | 1 | 0
Itching | 10 | 2 | 0 | 15 | 2 | 0 | 6 | <1 | 0
Burning | 3 | <1 | 0 | 8 | 2 | 0 | 2 | <1 | 0
Stinging | 2 | <1 | 0 | 6 | 1 | 0 | 1 | <1 | 0

*Mod. = Moderate

6.2 Postmarketing Experience

Anaphylaxis, as well as allergic reactions leading to hospitalizations, has been reported in postmarketing use of products containing clindamycin/benzoyl peroxide.
Because these reactions are reported voluntarily from a population of uncertain size, it is not always possible to reliably estimate their frequency or establish a causal relationship to drug exposure.

7 DRUG INTERACTIONS

7.1 Erythromycin

Clindamycin Phosphate and Benzoyl Peroxide Gel, 1.2% / 2.5% should not be used in combination with topical or oral erythromycin-containing products due to its clindamycin component. In vitro studies have shown antagonism between erythromycin and clindamycin. The clinical significance of this in vitro antagonism is not known.

7.2 Neuromuscular Blocking Agents

Clindamycin has been shown to have neuromuscular blocking properties that may enhance the action of other neuromuscular blocking agents. Therefore, Clindamycin Phosphate and Benzoyl Peroxide Gel, 1.2% / 2.5% should be used with caution in patients receiving such agents.

8 USE IN SPECIFIC POPULATIONS

8.1 Pregnancy

Pregnancy Category C.
There are no adequate and well-controlled studies in pregnant women treated with Clindamycin Phosphate and Benzoyl Peroxide Gel, 1.2% / 2.5%. Clindamycin Phosphate and Benzoyl Peroxide Gel, 1.2% / 2.5% should be used during pregnancy only if the potential benefit justifies the potential risk to the fetus.
Animal reproductive/developmental toxicity studies have not been conducted with Clindamycin Phosphate and Benzoyl Peroxide Gel, 1.2% / 2.5% or benzoyl peroxide. Developmental toxicity studies of clindamycin performed in rats and mice using oral doses of up to 600 mg/kg/day (240 and 120 times amount of clindamycin in the highest recommended adult human dose based on mg/m^2, respectively) or subcutaneous doses of up to 200 mg/kg/day (80 and 40 times the amount of clindamycin in the highest recommended adult human dose based on mg/m^2, respectively) revealed no evidence of teratogenicity.

8.3 Nursing Mothers

It is not known whether clindamycin is excreted in human milk after topical application of Clindamycin Phosphate and Benzoyl Peroxide Gel, 1.2% / 2.5%. However, orally and parenterally administered clindamycin has been reported to appear in breast milk. Because of the potential for serious adverse reactions in nursing infants, a decision should be made whether to use Clindamycin Phosphate and Benzoyl Peroxide Gel, 1.2% / 2.5% while nursing, taking into account the importance of the drug to the mother.

8.4 Pediatric Use

Safety and effectiveness of Clindamycin Phosphate and Benzoyl Peroxide Gel, 1.2% / 2.5% in pediatric patients under the age of 12 have not been evaluated.

8.5 Geriatric Use

Clinical trials of Clindamycin Phosphate and Benzoyl Peroxide Gel, 1.2% / 2.5% did not include sufficient numbers of subjects aged 65 and older to determine whether they respond differently from younger subjects.

11 DESCRIPTION

Clindamycin Phosphate and Benzoyl Peroxide Gel, 1.2% / 2.5% is a combination product with two active ingredients in a white to off-white, opaque, smooth, aqueous gel formulation intended for topical use. Clindamycin phosphate is a water-soluble ester of the semi-synthetic antibiotic produced by a 7(S)-chloro-substitution of the 7(R)-hydroxyl group of the parent antibiotic lincomycin.

The chemical name for clindamycin phosphate is Methyl 7 chloro-6,7,8-trideoxy- 6-(1-methyl-trans-4-propyl-L-2-pyrrolidinecarboxamido)-1-thio-L-threo a-D-galacto octopyranoside 2-(dihydrogen phosphate). The structural formula for clindamycin phosphate is represented below:
Clindamycin phosphate:

Molecular Formula: C18H34CIN2O8PS Molecular Weight: 504.97

Benzoyl peroxide is an antibacterial and keratolytic agent. The structural formula for benzoyl peroxide is represented below:
Benzoyl peroxide:

Molecular Formula: C14H10O4 Molecular Weight: 242.23

Clindamycin Phosphate and Benzoyl Peroxide Gel, 1.2% / 2.5% contains the following inactive ingredients: carbopol 980, poloxamer 182, polysorbate 80, propylene glycol, purified water and sodium hydroxide. Each gram of Clindamycin Phosphate and Benzoyl Peroxide Gel, 1.2% / 2.5% contains 1.2% of clindamycin phosphate which is equivalent to 1% clindamycin.

12 CLINICAL PHARMACOLOGY

12.1 Mechanisms of Action

Clindamycin: Clindamycin is a lincosamide antibacterial [See Microbiology (12.4)].
Benzoyl Peroxide: Benzoyl peroxide is an oxidizing agent with bacteriocidal and keratolytic effects but the precise mechanism of action is unknown.

12.3 Pharmacokinetics

The systemic absorption of clindamycin was investigated in an open-label, multiple-dose trial in 16 adult subjects with moderate to severe acne vulgaris treated with 1 gram of Clindamycin Phosphate and Benzoyl Peroxide Gel, 1.2% / 2.5% applied to the face once daily for 30 days. Twelve subjects (75%) had at least one quantifiable clindamycin plasma concentration above the lower limit of quantification (LOQ = 0.5 ng/mL) on Day 1 or Day 30. On Day 1, the mean (± standard deviation) peak plasma concentration (Cmax) was 0.78 ± 0.22 ng/mL max (n=9 with measurable concentrations), and the mean AUC0-t was 5.29 ± 0.81 0-t h.ng/mL (n=4). On Day 30, the mean Cmax was 1.22 ± 0.88 ng/mL (n=10), and the max mean AUC0-t was 8.42 ± 6.01 h.ng/mL (n=6). Clindamycin plasma concentrations were below LOQ in all subjects at 24 hours post-dose on the three tested days (Day 1, 15, and 30).
Benzoyl peroxide has been shown to be absorbed by the skin where it is converted to benzoic acid.

12.4 Microbiology

Clindamycin binds to the 50S ribosomal subunits of susceptible bacteria and prevents elongation of peptide chains by interfering with peptidyl transfer, thereby suppressing bacterial protein synthesis.

Clindamycin and benzoyl peroxide individually have been shown to have in vitro activity against Propionibacterium acnes, an organism which has been associated with acne vulgaris; however, the clinical significance of this activity against P. acnes is not known.

P. acnes resistance to clindamycin has been documented. Resistance to clindamycin is often associated with resistance to erythromycin.

13 NONCLINICAL TOXICOLOGY

13.1 Carcinogenesis, Mutagenesis, Impairment of Fertility

Carcinogenicity, mutagenicity and impairment of fertility testing of Clindamycin Phosphate and Benzoyl Peroxide Gel, 1.2% / 2.5% have not been performed.
Benzoyl peroxide has been shown to be a tumor promoter and progression agent in a number of animal studies. Benzoyl peroxide in acetone at doses of 5 and 10 mg administered topically twice per week for 20 weeks induced skin tumors in transgenic Tg.AC mice. The clinical significance of this is unknown.
Carcinogenicity studies have been conducted with a gel formulation containing 1% clindamycin and 5% benzoyl peroxide. In a 2-year dermal carcinogenicity study in mice, treatment with the gel formulation at doses of 900, 2700, and 15000 mg/kg/day (1.8, 5.4, and 30 times amount of clindamycin and 3.6, 10.8, and 60 times amount of benzoyl peroxide in the highest recommended adult human dose of 2.5 g Clindamycin Phosphate and Benzoyl Peroxide Gel, 1.2% / 2.5% based on mg/m2, respectively) did not cause any increase in tumors. However, topical treatment with a different gel formulation containing 1% clindamycin and 5% benzoyl peroxide at doses of 100, 500, and 2000 mg/kg/day caused a dose-dependent increase in the incidence of keratoacanthoma at the treated skin site of male rats in a 2-year dermal carcinogenicity study in rats. In an oral (gavage) carcinogenicity study in rats, treatment with the gel formulation at doses of 300, 900 and 3000 mg/kg/day (1.2, 3.6, and 12 times amount of clindamycin and 2.4, 7.2, and 24 times amount of benzoyl peroxide in the highest recommended adult human dose of 2.5 g Clindamycin Phosphate and Benzoyl Peroxide Gel, 1.2% / 2.5% based on mg/m2, respectively) for up to 97 weeks did not cause any increase in tumors. In a 52-week dermal photocarcinogenicity study in hairless mice, (40 weeks of treatment followed by 12 weeks of observation), the median time to onset of skin tumor formation decreased and the number of tumors per mouse increased relative to controls following chronic concurrent topical administration of the higher concentration benzoyl peroxide formulation (5000 and 10000 mg/kg/day, 5 days/week) and exposure to ultraviolet radiation.
Clindamycin phosphate was not genotoxic in the human lymphocyte chromosome aberration assay. Benzoyl peroxide has been found to cause DNA strand breaks in a variety of mammalian cell types, to be mutagenic in S. typhimurium tests by some but not all investigators, and to cause sister chromatid exchanges in Chinese hamster ovary cells.
Fertility studies have not been performed with Clindamycin Phosphate and Benzoyl Peroxide Gel, 1.2% / 2.5% or benzoyl peroxide, but fertility and mating ability have been studied with clindamycin. Fertility studies in rats treated orally with up to 300 mg/kg/day of clindamycin (approximately 120 times the amount of clindamycin in the highest recommended adult human dose of 2.5 g Clindamycin Phosphate and Benzoyl Peroxide Gel, 1.2% / 2.5%, based on mg/m^2) revealed no effects on fertility or mating ability.

14 CLINICAL STUDIES

The safety and efficacy of once daily use of Clindamycin Phosphate and Benzoyl Peroxide Gel, 1.2% / 2.5% were assessed in two 12-week multi center, randomized, blinded trials in subjects 12 years and older with moderate to severe acne vulgaris. The two trials were identical in design and compared Clindamycin Phosphate and Benzoyl Peroxide Gel, 1.2% / 2.5% to clindamycin in the vehicle gel, benzoyl peroxide in the vehicle gel, and the vehicle gel alone.

The co-primary efficacy variables were:

(1) Mean absolute change from baseline at week 12 in
• Inflammatory lesion counts
• Non-inflammatory lesion counts

(2) Percent of subjects who had a two grade improvement from baseline on an Evaluator's Global Severity (EGS) score.

The EGS scoring scale used in all of the clinical trials for Clindamycin Phosphate and Benzoyl Peroxide Gel, 1.2% / 2.5% is as follows:

Grade | Description
Clear | Normal, clear skin with no evidence of acne vulgaris
Almost Clear | Rare non-inflammatory lesions present, with rare non-inflamed papules (papules must be resolving and may be hyperpigmented, though not pink-red)
Mild | Some non-inflammatory lesions are present, with few inflammatory lesions (papules/pustules only; no nodulocystic lesions)
Moderate | Non-inflammatory lesions predominate, with multiple inflammatory lesions evident: several to many comedones and papules/pustules, and there may or may not be one small nodulo-cystic lesion
Severe | Inflammatory lesions are more apparent, many comedones and papules/pustules, there may or may not be a few nodulocystic lesions
Very Severe | Highly inflammatory lesions predominate, variable number of comedones, many papules/pustules and many nodulocystic lesions

The results of Trial 1 at week 12 are presented in Table 2:
Table 2: Trial 1 Results

Trial 1 | Clindamycin Phosphate and Benzoyl Peroxide Gel, 1.2% / 2.5% N = 399 | Clindamycin Gel N = 408 | Benzoyl Peroxide Gel N = 406 | Vehicle Gel N = 201
EGSS Clear or Almost Clear 2 grade reduction from baseline | 115 (29%) 131 (33%) | 84 (21%) 100 (25%) | 76 (19%) 96 (24%) | 29 (14%) 38 (19%)
Inflammatory Lesions: Mean absolute change Mean percent (%) reduction | 14.8 55.0% | 12.2 47.1% | 13.0 49.3% | 9.0 34.5%
Non-Inflammatory Lesions: Mean absolute change Mean percent (%) reduction | 22.1 45.3% | 17.9 38.0% | 20.6 40.2% | 13.2 28.6%

The results of Trial 2 at week 12 are presented in Table 3:

Table 3: Trial 2 Results

Trial 2 | Clindamycin Phosphate and Benzoyl Peroxide Gel, 1.2% / 2.5% N = 398 | Clindamycin Gel N = 404 | Benzoyl Peroxide Gel N = 403 | Vehicle Gel N = 194
EGSS Clear or Almost Clear 2 grade reduction from baseline | 113 (28%) 147 (37%) | 94 (23%) 114 (28%) | 94 (23%) 114 (28%) | 21 (11%) 27 (14%)
Inflammatory Lesions: Mean absolute change Mean percent (%) reduction | 13.7 54.2% | 11.3 45.3% | 11.2 45.7% | 5.7 23.3%
Non-Inflammatory Lesions: Mean absolute change Mean percent (%) reduction | 19.0 41.2% | 14.9 34.3% | 15.2 34.5% | 8.3 19.2%

16 HOW SUPPLIED/STORAGE AND HANDLING

16.1 How Supplied

Clindamycin Phosphate and Benzoyl Peroxide Gel, 1.2% / 2.5% is supplied as a 50 g pump (NDC 21922-074-40).

16.2 Dispensing Instructions for the Pharmacist

• Dispense Clindamycin Phosphate and Benzoyl Peroxide Gel, 1.2% / 2.5% with a 10 week expiration date.
• Specify “Store at room temperature up to 25°C (77°F). Do not freeze.”

16.3 Storage and Handling

• PHARMACIST: Prior to Dispensing: Store in a refrigerator, 2°C to 8°C (36°F to 46°F).
• PATIENT: Store at room temperature at or below 25°C (77°F).
• Protect from freezing.
• Keep out of the reach of children.
• Keep container tightly closed.

17 PATIENT COUNSELING INFORMATION

See FDA-approved patient labeling (Patient Information).
• Patients who develop allergic reactions such as severe swelling or shortness of breath should discontinue use and contact their physician immediately.
• Clindamycin Phosphate and Benzoyl Peroxide Gel, 1.2% / 2.5% may cause irritation such as erythema, scaling, itching, or burning, especially when used in combination with other topical acne therapies.
• Excessive or prolonged exposure to sunlight should be limited. To minimize exposure to sunlight, a hat or other clothing should be worn. Sunscreen may also be used.
• Clindamycin Phosphate and Benzoyl Peroxide Gel, 1.2% / 2.5% may bleach hair or colored fabric.

Manufactured by:
Encube Ethicals Pvt. Ltd.
Plot No. C-1, Madkaim
Industrial Estate, Madkaim,
Post: Mardol, Ponda,
Goa - 403 404, India.

Distributed by:
Encube Ethicals, Inc.
200 Meredith Drive,
Suite 202 Durham,
NC 27713 USA

Revised: 07/2023

PATIENT INFORMATION

Clindamycin Phosphate and Benzoyl Peroxide Gel, 1.2% / 2.5%

IMPORTANT: For use on skin only (topical use). Do not get Clindamycin Phosphate and Benzoyl Peroxide Gel, 1.2% / 2.5% in your mouth, eyes, or vagina, or on your lips.

Read the Patient Information that comes with Clindamycin Phosphate and Benzoyl Peroxide Gel, 1.2% / 2.5% before you start using it and each time you get a refill. There may be new information. This leaflet does not take the place of talking with your doctor about your medical condition or your treatment.
What is Clindamycin Phosphate and Benzoyl Peroxide Gel, 1.2% / 2.5%?
Clindamycin Phosphate and Benzoyl Peroxide Gel, 1.2% / 2.5% is a prescription medicine used on the skin (topical) to treat acne vulgaris in people 12 years and older. Clindamycin Phosphate and Benzoyl Peroxide Gel, 1.2% / 2.5% contains clindamycin phosphate and benzoyl peroxide.
It is not known if Clindamycin Phosphate and Benzoyl Peroxide Gel, 1.2% /2.5% is safe and effective for use longer than 12 weeks.
It is not known if Clindamycin Phosphate and Benzoyl Peroxide Gel, 1.2% / 2.5% is safe and effective in children under 12 years of age.
Who should not use Clindamycin Phosphate and Benzoyl Peroxide Gel, 1.2% / 2.5%?
Do not use Clindamycin Phosphate and Benzoyl Peroxide Gel, 1.2% / 2.5% if you have:
• Crohn's disease
• ulcerative colitis
• had inflammation of the colon (colitis), or severe diarrhea with past antibiotic use
Talk with your doctor if you are not sure if you have one of these conditions.
What should I tell my doctor before using Clindamycin Phosphate and Benzoyl Peroxide Gel, 1.2% / 2.5%?
Before using Clindamycin Phosphate and Benzoyl Peroxide Gel, 1.2% / 2.5%, tell your doctor about all of your medical conditions,
including if you:
• have any allergies.
• have any other medical conditions
• are pregnant or planning to become pregnant. It is not known if Clindamycin Phosphate and Benzoyl Peroxide Gel, 1.2% / 2.5% will harm your unborn baby.
• are breastfeeding or plan to breast feed. It is not known if Clindamycin Phosphate and Benzoyl Peroxide Gel, 1.2% / 2.5% passes into your breast milk. One of the medicines in Clindamycin Phosphate and Benzoyl Peroxide Gel, 1.2% / 2.5% contains clindamycin.
Clindamycin when taken by mouth or by injection has been reported to appear in breast milk. You and your doctor should decide whether you will use Clindamycin Phosphate and Benzoyl Peroxide Gel, 1.2% / 2.5% while breast-feeding.
Tell your doctor about all the medicines and skin products you use. Especially tell your doctor if you will have surgery with general anesthesia. One of the medicines in Clindamycin Phosphate and Benzoyl Peroxide Gel, 1.2% / 2.5% (clindamycin) can affect how certain medicines work when used in general anesthesia.
• Clindamycin Phosphate and Benzoyl Peroxide Gel. 1.2% / 2.5% should not be used with products that contain erythromycin.
• Other skin and topical acne products may increase the irritation of your skin when used with Clindamycin Phosphate and Benzoyl Peroxide Gel, 1.2% / 2.5%.
Know the medicines you take. Keep a list of them and show it to your doctor and pharmacist when you get a new medicine.
How should I use Clindamycin Phosphate and Benzoyl Peroxide Gel, 1.2% / 2.5%?
• Use Clindamycin Phosphate and Benzoyl Peroxide Gel, 1.2% / 2.5% exactly as prescribed.
• Your doctor will tell you how long to use Clindamycin Phosphate and Benzoyl Peroxide Gel, 1.2% / 2.5%.
• Throw away (discard) any unused Clindamycin Phosphate and Benzoyl Peroxide Gel, 1.2% / 2.5%.
Instructions for applying Clindamycin Phosphate and Benzoyl Peroxide Gel, 1.2% / 2.5%
• Apply Clindamycin Phosphate and Benzoyl Peroxide Gel, 1.2% /2.5% to your face one time each day as prescribed.
1. Before you apply Clindamycin Phosphate and Benzoyl Peroxide Gel, 1.2% / 2.5%, wash your face gently with a mild soap, rinse with warm water, and pat your skin dry.
2. To apply Clindamycin Phosphate and Benzoyl Peroxide Gel, 1.2% / 2.5% to your face, use the pump to dispense one pea-sized amount of Clindamycin Phosphate and Benzoyl Peroxide Gel, 1.2% / 2.5% onto your fingertip.

See Figure 1. One pea-sized amount of Clindamycin Phosphate and Benzoyl Peroxide Gel, 1.2% / 2.5% should be enough to cover your entire face.

3. Dot the one pea-sized amount of Clindamycin Phosphate and Benzoyl Peroxide Gel, 1.2% / 2.5% onto six areas of your face (chin, left cheek, right cheek, nose, left forehead, right forehead). See Figure 2.

4. After applying the Clindamycin Phosphate and Benzoyl Peroxide Gel, 1.2% / 2.5% this way, spread the gel over your face and gently rub it in. it is important to spread the gel ove your whole face.
5. Wash your hands with soap and water after applying Clindamycin Phosphate and Benzoyl Peroxide Gel, 1.2% / 2.5%.
6. If your doctor tells you to put Clindamycin Phosphate and Benzoyl Peroxide Gel, 1.2% / 2.5% on other areas of your skin with acne, be sure to ask how much you should use.
7. Do not gel Clindamycin Phosphate and Benzoyl Peroxide Gel, 1.2% / 2.5% in your mouth, eyes, or nose, or on your lips. If this occurs, rinse the affected area with warm water and call your doctor right away if the area becomes very red, itchy, tender, or swollen.
8. Do not gel Clindamycin Phosphate and Benzoyl Peroxide Gel, 1.2% / 2.5% on cuts or open wounds.
9. Do not use more Clindamycin Phosphate and Benzoyl Peroxide Gel, 1.2% / 2.5% than prescribed.
What should I avoid while using Clindamycin Phosphate and Benzoyl Peroxide Gel, 1.2% I 2.5%?
• Limit your time in sunlight Avoid using tanning beds or sun lamps. If you have to be in sunlight, wear a wide-brimmed hat or other protective clothing, and a sunscreen with SPF 15 rating or higher. Your doctor can give you more information about why this is important.
• Do not wash your face more than 2 to 3 times a day. Washing your face too often or scrubbing it may make your acne worse.
• Avoid getting Clindamycin Phosphate and Benzoyl Peroxide Gel, 1.2% / 2.5% in your hair or on colored fabric. Clindamycin Phosphate and Benzoyl Peroxide Gel, 1.2% / 2.5% may bleach hair or colored fabric.
What are possible side effects with Clindamycin Phosphate and Benzoyl Peroxide Gel, 1.2% / 2.5%?
Clindamycin Phosphate and Benzoyl Peroxide Gel, 1.2% / 2.5% can cause serious side effects including:
• Inflammation of the colon (colitis).
Stop using Clindamycin Phosphate and Benzoyl Peroxide Gel, 1.2% / 2.5% and call your doctor right away if you have severe watery diarrhea, or bloody diarrhea.
• Allergic reactions. Stop using Clindamycin Phosphate and Benzoyl Peroxide Gel, 1.2% / 2.5%. call your doctor and get help right away if you have any of the following symptoms:
o severe itching
o swelling of your face, eyes, lips, tongue or throat
o trouble breathing
Common side effects with Clindamycin Phosphate and Benzoyl Peroxide Gel, 1.2% / 2.5% include:
• Skin irritation. Stop using Clindamycin Phosphate and Benzoyl Peroxide Gel, 1.2% /2.5% and call your doctor if you have a skin rash or your skin becomes very red, itchy or swollen.
Talk to your doctor about any side effect that bothers you or that does not go away.
These are not all the possible side effects with Clindamycin Phosphate and Benzoyl Peroxide Gel, 1.2% / 2.5%. Ask your doctor or pharmacist for more information.
Call your doctor for medical advice about side effects. You may report side effects to FDA at 1-800-FDA-1088 or www.fda.govfrnedwatch. You may also report side effects to Encube Ethicals Pvt Lid. al 1-833-285-4151.
How should I store Clindamycin Phosphate and Benzoyl Peroxide Gel, 1.2% / 2.5%?
• Store Clindamycin Phosphate and Benzoyl Peroxide Gel, 1.2% / 2.5% at room temperature at or below 25°C (77°F).
• The expiration date of Clindamycin Phosphate and Benzoyl Peroxide Gel, 1.2% / 2.5% is 10 weeks from the date you fill your prescription.
• Safely throw away expired Clindamycin Phosphate and Benzoyl Peroxide Gel, 1.2% / 2.5%.
• Do not freeze.
• Keep the container tightly closed.
Keep Clindamycin Phosphate and Benzoyl Peroxide Gel, 1.2% / 2.5% and all medicines out of the reach of children.
General information about Clindamycin Phosphate and Benzoyl Peroxide Gel, 1.2% / 2.5%
Medicines are sometimes prescribed for conditions that are not mentioned in Patient Information leaflets. Do not use Clindamycin Phosphate and Benzoyl Peroxide Gel, 1.2% / 2.5% for a condition for which it was not prescribed.
Do not give Clindamycin Phosphate and Benzoyl Peroxide Gel, 1.2% / 2.5% to other people, even if they have the same condition you have. It may harm them.
This leaflet summarizes the most important information about Clindamycin Phosphate and Benzoyl Peroxide Gel, 1.2% / 2.5%. If you would like more information, talk with your doctor. You can also ask your doctor or pharmacist for information about Clindamycin Phosphate and Benzoyl Peroxide Gel, 1.2% / 2.5% that is written for healthcare professionals.
For more information about Clindamycin Phosphate and Benzoyl PeroxideGel.1.2% / 2.5%, call 1-833-285-4151.
What are the ingredients in Clindamycin Phosphate and Benzoyl Peroxide Gel, 1.2% / 2.5%?
Active Ingredients: clindamycin phosphate 1.2% and benzoyl peroxide 2.5%
Inactive Ingredients: carbopol 980, poloxamer 182, polysorbate 80, propylene glycol, purified water and sodium hydroxide
Manufactured by:
Encube Ethicals Pvt. Ltd.Plot No. C-1, Madkaim Industrial Estate, Madkaim,
Post: Mardol, Ponda, Goa - 403 404, India.
Distributed by:
Encube Ethicals, Inc.200 Meredith Drive, Suite 202 Durham,
NC 27713 USA
This Patient Information has been approved by the U.S. Food and Drug Administration.

Revised: 07/2023

PACKAGE LABEL.PRINCIPAL DISPLAY PANEL

Clindamycin Phosphate and Benzoyl Peroxide Gel, 1.2%/ 2.5% : 50 gram pump

Carton Label-

NDC21922-074-40

Clindamycin Phosphate and Benzoyl Peroxide Gel, 1.2% / 2.5%

FOR TOPICAL USE ONLY

One premixed 50-gram pump dispenser

RX only